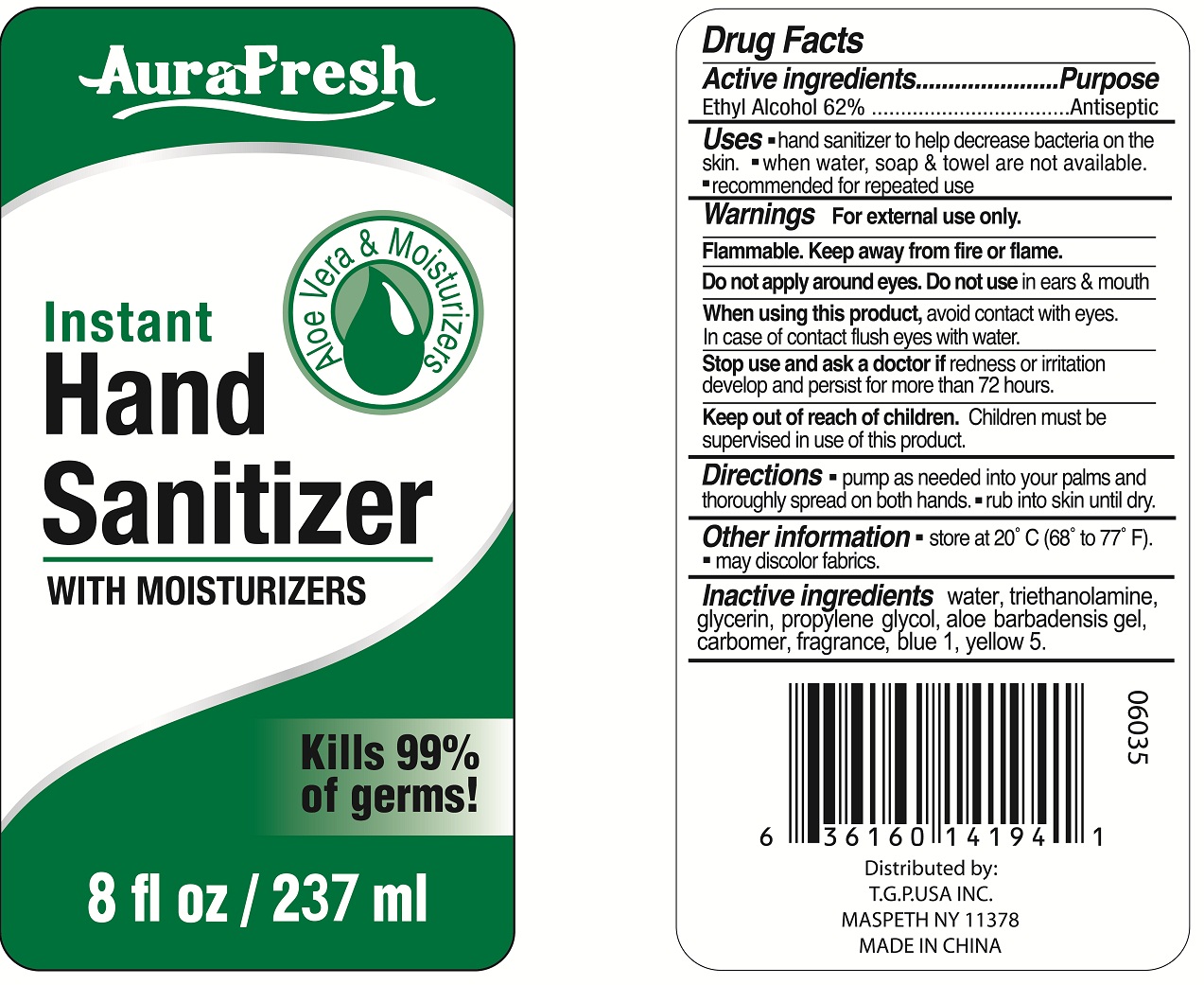 DRUG LABEL: aurafresh instant hand sanitizer with moisturizers
NDC: 40104-282 | Form: GEL
Manufacturer: Ningbo Pulisi Daily Chemical Products Co., Ltd.
Category: otc | Type: HUMAN OTC DRUG LABEL
Date: 20170810

ACTIVE INGREDIENTS: alcohol 62 mL/100 mL
INACTIVE INGREDIENTS: WATER; PROPYLENE GLYCOL; ALOE VERA LEAF; CARBOMER 934; GLYCERIN; .ALPHA.-TOCOPHEROL ACETATE, D-; TROLAMINE; FD&C BLUE NO. 1; FD&C YELLOW NO. 5

Drug facts

Active ingredient Purpose

Ethyl Alcohol 62% ... Antiseptic

PURPOSE

Hand sanitizer to help decrease bacteria on the skin.

KEEP OUT OF REACH OF CHILDREN

If swallowed, get medical help or contact local poison control center right away.

Children must be supervised in use of this product.

INDICATIONS AND USAGE

keep out of eyes

when water, soap and towel are not available

WARNINGS

For external use only.
Flammable. Keep away from hear or flame.

Do not apply around eyes; Do not use in ears and mouth. When using this products, avoid contact with eyes. In case of contact, flush eyes with water.

Stop using and ask a doctor, if irritation and redness develops, if condition persists for more than 72 hours, consult a doctor.

DOSAGE AND ADMINISTRATION

Pump as needed into your palms and thoroughly spread on both hands, and rub the skin until dry.

INACTIVE INGREDIENT

Water, Carbomer, Glycerin, Propylene Glycol, Triethanolamine, Aloe Barbadensis Leaf Juice, Tocopheryl Acetate, Fragrance